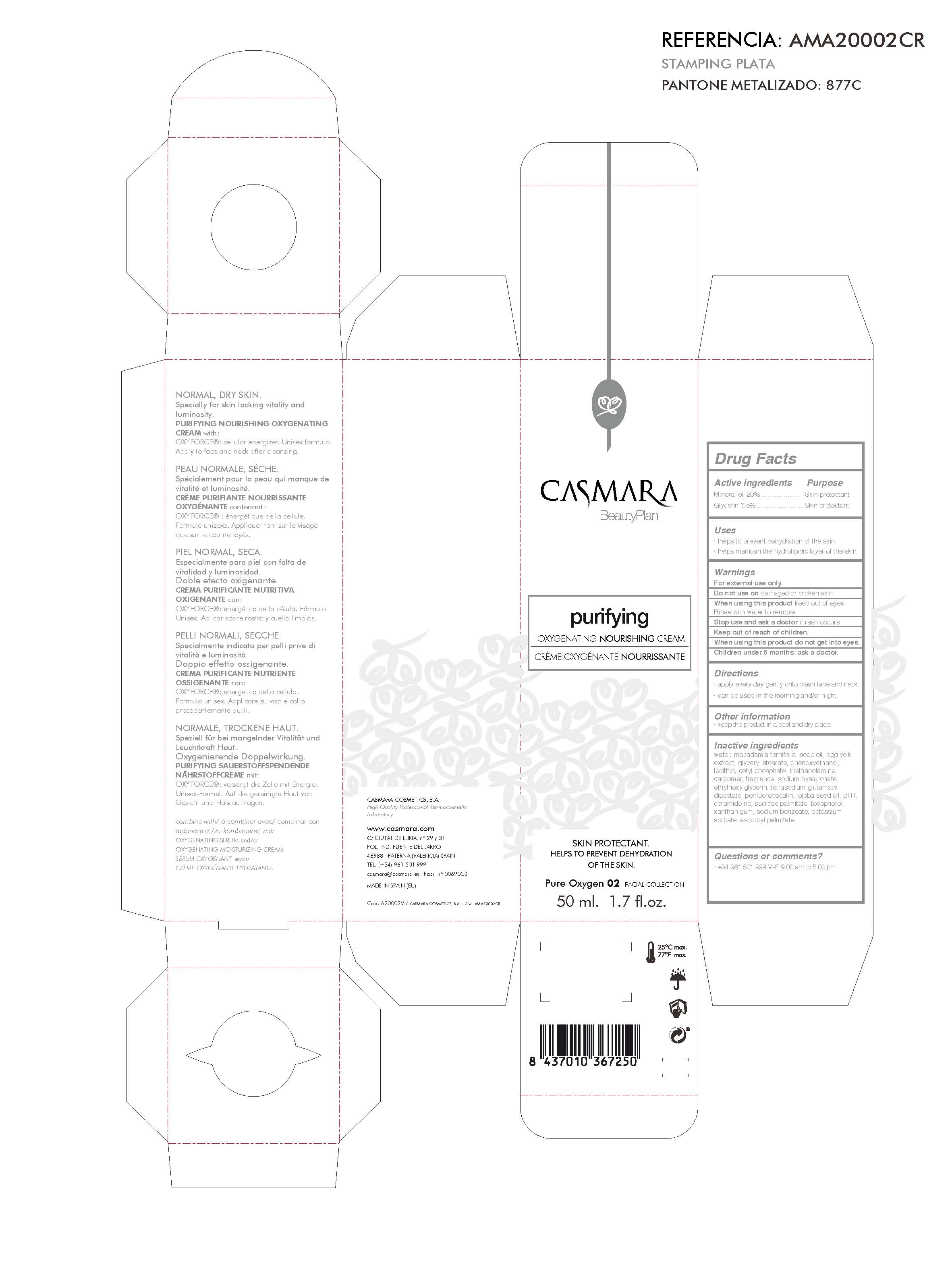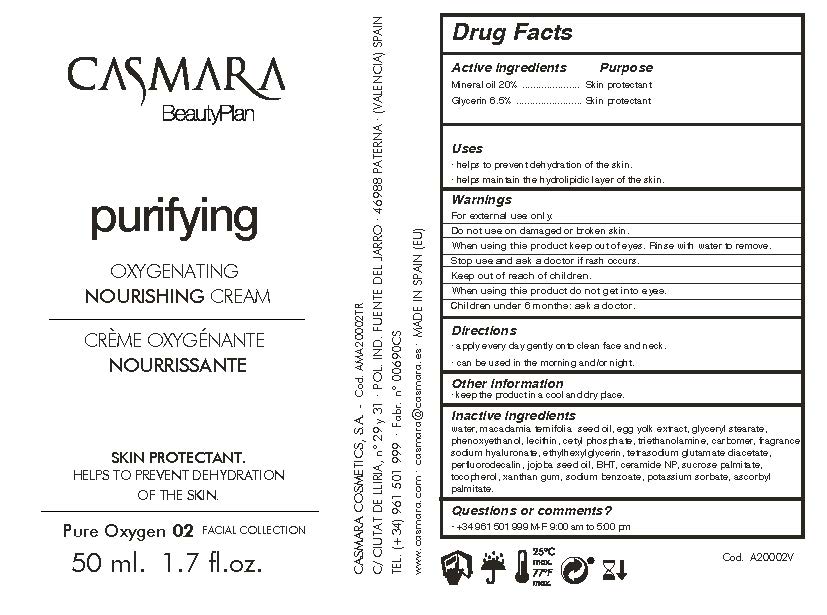 DRUG LABEL: Nourishing Cream
NDC: 20151-084 | Form: CREAM
Manufacturer: Casmara Cosmetics, SA
Category: otc | Type: HUMAN OTC DRUG LABEL
Date: 20170222

ACTIVE INGREDIENTS: MINERAL OIL 20 mg/1 mL; GLYCERIN 6.5 mg/1 mL
INACTIVE INGREDIENTS: MACADAMIA OIL 5.99 mg/1 mL; EGG YOLK 2 mg/1 mL; PHENOXYETHANOL 0.9 mg/1 mL; POTASSIUM SORBATE 0.001 mg/1 mL; ASCORBYL PALMITATE 0.0005 mg/1 mL; BUTYLATED HYDROXYTOLUENE 0.01 mg/1 mL; GLYCERYL STEARATE SE 2 mg/1 mL; WATER 59.7 mg/1 mL; LECITHIN, SOYBEAN 0.625 mg/1 mL; CETYL PHOSPHATE 0.625 mg/1 mL; TROLAMINE 0.6 mg/1 mL; CARBOXYPOLYMETHYLENE 0.4 mg/1 mL; PEG-9 DIGLYCIDYL ETHER/SODIUM HYALURONATE CROSSPOLYMER 0.1 mg/1 mL; ETHYLHEXYLGLYCERIN 0.1 mg/1 mL; TETRASODIUM GLUTAMATE DIACETATE 0.094 mg/1 mL; PERFLUNAFENE 0.035 mg/1 mL; SIMMONDSIA CHINENSIS SEED 0.015 mg/1 mL; CERAMIDE NS DILAURATE 0.006 mg/1 mL; SUCROSE PALMITATE 0.006 mg/1 mL; TOCOPHEROL 0.003 mg/1 mL; XANTHAN GUM 0.001 mg/1 mL; SODIUM BENZOATE 0.001 mg/1 mL

PURIFYING OXYGENATING NOURISHING CREAM

USES

. helps to prevent dehydration of the skin

. heps maintain the hydrolipidic layer of the skin.

USES

.helps to precent dehydration of the skin

.helps maintain the hydrolipidic layer of the skin

ACTIVE INGREDIENTS

ACTIVE INGREDIENTS PURPOSE

Mineral Oil 20%.................. Skin protectant

Glycerin 6.5%.................... Skin Protectant

WARNINGS

For external use only.

Do not use on damaged or broken skin.

When using this product keep out of eyes. Rinse with water to remove.

Stop use and ask a doctor if rash occurs.

Keep out of reach of children.

When using this product do not get into eyes.

Children under 6 months: ask a doctor

Children under 6 months: ask a doctor

Stop use and ask a doctor if rash occurs.

Keep out of reach of children.

DIRECTIONS

. apply every day gently onto clean face and neck.

. can be used in the morning and/or night.

DIRECTIONS

. apply every day gently onto clean face and neck.

. can be used in the morning and/or night.

OTHER INFORMATION

. keep the product in a cool and dry place

INACTIVE INGREDIENTS

Water, Macadamia ternifolia seed oil, Egg yolk extract, Glyceryl stearate, Phenoxyethanol, Lecithin , Cetyl phosphate, Triethanolamine, Carbomer, Fragrance, Sodium hyaluronate, Ethylhexylglycerin, Tetrasodium glutamate diacetate, Perfluorodecalin, Jojoba seed oil, BHT, Ceramide NP, Sucrose Palmitate, Tocopherol, Xanthan gum, Sodium benzoate, Potassium sorbate, Ascorbyl palmitate

QUESTIONS OR COMMENTS?

+ 34 961 501 999

M-F 9:00 am to 5:00 pm

PURIFYING OXYGENATING NOURISHING CREAM

Purifying Nourishing Cream